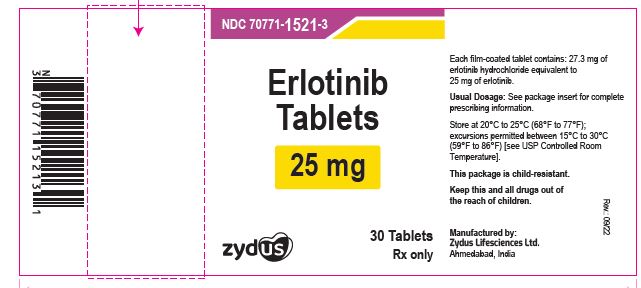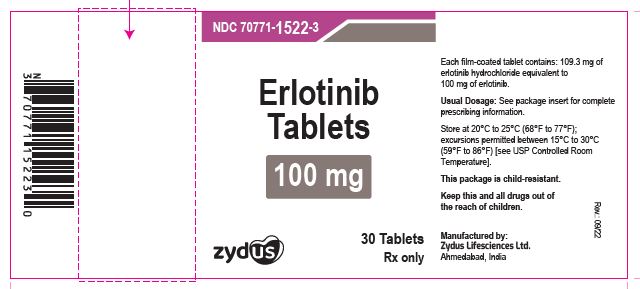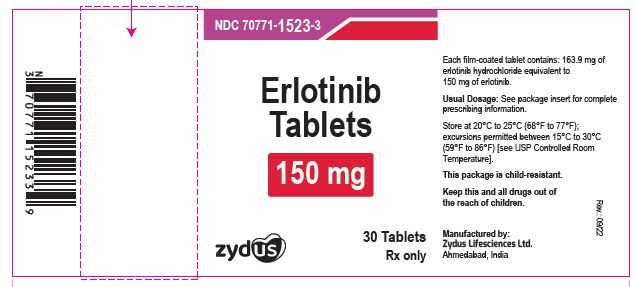 DRUG LABEL: Erlotinib
NDC: 70771-1521 | Form: TABLET, FILM COATED
Manufacturer: Zydus Lifesciences Limited
Category: prescription | Type: HUMAN PRESCRIPTION DRUG LABEL
Date: 20241128

ACTIVE INGREDIENTS: ERLOTINIB HYDROCHLORIDE 25 mg/1 1
INACTIVE INGREDIENTS: CROSPOVIDONE (120 .MU.M); HYPROMELLOSE 2910 (6 MPA.S); LACTOSE MONOHYDRATE; MAGNESIUM STEARATE; MICROCRYSTALLINE CELLULOSE 101; MICROCRYSTALLINE CELLULOSE 102; POLYETHYLENE GLYCOL 4000; SILICON DIOXIDE; SODIUM LAURYL SULFATE; TALC; TITANIUM DIOXIDE

Erlotinib Tablets

PACKAGE LABEL.PRINCIPAL DISPLAY PANEL

Erlotinib Tablets, 25 mg

30 tablets

NDC 70771-1521-3

Rx only

Erlotinib Tablets, 100 mg

30 tablets

NDC 70771-1522-3

Rx only

Erlotinib Tablets, 150 mg

30 tablets

NDC 70771-1523-3

Rx only